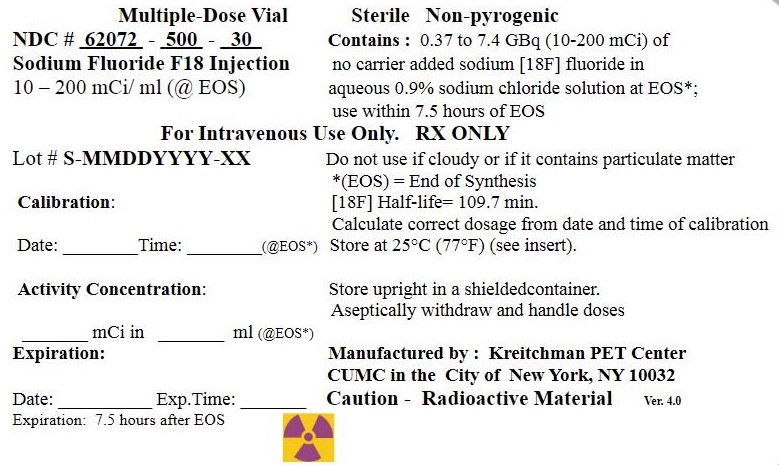 DRUG LABEL: Sodium Fluoride
NDC: 62072-500 | Form: INJECTION
Manufacturer: Kreitchman PET Center
Category: prescription | Type: HUMAN PRESCRIPTION DRUG LABEL
Date: 20260127

ACTIVE INGREDIENTS: SODIUM FLUORIDE F-18 200 mCi/1 mL
INACTIVE INGREDIENTS: SODIUM CHLORIDE

HIGHLIGHTS OF PRESCRIBING INFORMATION

These highlights do not include all the information needed to use Sodium Fluoride F 18 Injection safely and effectively. See full prescribing information for Sodium Fluoride F 18 Injection.
SODIUM FLUORIDE F 18 INJECTION
For Intravenous Use
Initial U.S. Approval: 2016

3 DOSAGE FORMS AND STRENGTHS

Multiple-dose vial containing 370-7,400 MBq/mL (10–200 mCi/mL) at EOS reference time of no-carrier-added sodium fluoride F18 in aqueous 0.9% sodium chloride solution(3). Sodium Fluoride F 18 Injection is a clear, colorless, sterile, pyrogen-free and preservative-free solution for intravenous administration.

6 ADVERSE REACTIONS

No adverse reactions have been reported for Sodium Fluoride F 18 Injection based on a review of the published literature, publicly available reference sources, and adverse drug reaction reporting systems(6).

To report SUSPECTED ADVERSE REACTIONS, contact Kreitchman PET Center at 1-212-305-0081 or FDA at 1-800-FDA-1088 or www.fda.gov/medwatch.

FULL PRESCRIBING INFORMATION

3 DOSAGE FORMS AND STRENGTHS

Multiple-dose vial containing 370-7,400 MBq/mL (10–200 mCi/mL)at EOS reference time of no-carrier-added sodium fluoride F18 in aqueous 0.9% sodium chloride solution. Sodium Fluoride F 18 Injection is a clear, colorless, sterile, pyrogen-free and preservative-free solution for intravenous administration.

6 ADVERSE REACTIONS

No adverse reactions have been reported for Sodium Fluoride F 18 Injection based on a review of the published literature, publicly available reference sources, and adverse drug reaction reporting systems. However, the completeness of these sources is not known.

11 DESCRIPTION

11.1 Chemical Characteristics

Sodium Fluoride F 18 Injection is a positron emitting radiopharmaceutical, containing no-carrier-added, radioactive fluoride F18 that is used for diagnostic purposes in conjunction with PET imaging. It is administered by intravenous injection. The active ingredient, sodium fluoride F18, has the molecular formula Na[18F] with a molecular weight of 40.99, and has the following chemical structure:

Na^+18F^-

Sodium Fluoride F 18 Injection is provided as a ready-to-use, isotonic, sterile, pyrogen-free, preservative-free, clear and colorless solution. Each mL of the solution contains between 370 MBq to 7,400 MBq (10 mCi to 200 mCi) sodium fluoride F18, at the EOS reference time, in 0.9% aqueous sodium chloride. The pH of the solution is between 4.5 and 8. The solution is presented in 30 mL multiple- dose glass vials with variable total volume and total radioactivity in each vial.

11.2 Physical Characteristics

Fluoride F18 decays by positron (β+) emission and has a half-life of 109.7 minutes. Ninety-seven percent of the decay results in emission of a positron with a maximum energy of 633 keV and 3% of the decay results in electron capture with subsequent emission of characteristic X-rays of oxygen. The principal photons useful for diagnostic imaging are the 511 keV gamma photons, resulting from the interaction of the emitted positron with an electron (Table 2). Fluorine F18 atom decays to stable ^18O-oxygen.

Table 2: Principal Emission Data for Fluoride F18
Radiation/Emission | % per Disintegration | Mean Energy
Positron (β+) | 96.73 | 249.8 keV
Gamma (±) [Produced by positron annihilation [3] Kocher, D.C. Radioactive Decay Data Tables DOE/TIC-11026, 69, 1981.] | 193.46 | 511.0 keV

The specific gamma ray constant (point source air kerma coefficient) for fluoride F18 is 5.7 R/hr/mCi (1.35 x 10 ^-6 Gy/hr/kBq) at 1 cm. The half-value layer (HVL) for the 511 keV photons is 4 mm lead (Pb). A range of values for the attenuation of radiation results from the interposition of various thickness of Pb. The range of attenuation coefficients for this radionuclide is shown in Table 3. For example, the interposition of an 8 mm thickness of Pb with a coefficient of attenuation of 0.25 will decrease the external radiation by 75%.

Table 3:Radiation Attenuation of 511 keV Photons by Lead (Pb) Shielding
Shield Thickness (Pb) mm | Coefficient of Attenuation
0 | 0.00
4 | 0.50
8 | 0.25
13 | 0.10
26 | 0.01
39 | 0.001
52 | 0.0001

Table 4 lists the fraction of radioactivity remaining at selected time intervals from the calibration time. This information may be used to correct for physical decay of the radionuclide.

Table 4: Physical Decay Chart for Fluoride F18
Time Since Calibration | Fraction Remaining
0 [Calibration time] | 1.00
15 minutes | 0.909
30 minutes | 0.826
60 minutes | 0.683
110 minutes | 0.500
220 minutes | 0.250
440 minutes | 0.060
12 hours | 0.011
24 hours | 0.0001

16 HOW SUPPLIED

Sodium Fluoride F 18 Injection is supplied in a multiple-dose Type I glass vial with (elastomeric) stopper and aluminum crimp seal containing between 370-7,400 MBq/mL (10 to 200 mCi/mL) of no-carrier-added sodium fluoride F18, at the EOS reference time, in aqueous 0.9% sodium chloride solution. The total volume and total radioactivity per vial are variable. Each vial is enclosed in a shielding container of appropriate thickness.

The product is available in a 30 mL vial configuration with a variable fill volume. The NDC number is:
62702-500-30 (30 mL)

Storage

Store at 25°C (77°F); excursions permitted to 15–30°C (59–86°F). Use the solution within 8 hours of the EOS reference time.

Handling

Receipt, transfer, handling, possession, or use of this product is subject to the radioactive material regulations and licensing requirements of the U.S. Nuclear Regulatory Commission, Agreement States or Licensing States as appropriate.

Manufactured by: Kreitchman PET Center, 722 W 171st St., New York, NY 10032